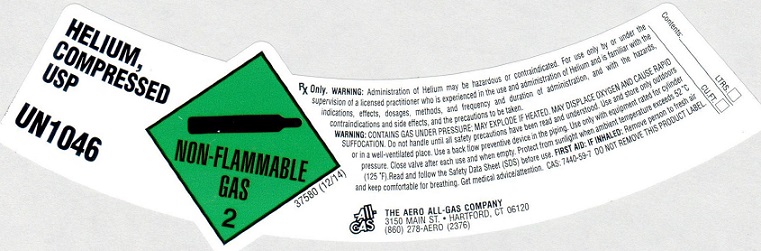 DRUG LABEL: Helium
NDC: 10014-014 | Form: GAS
Manufacturer: Aero All Gas Company
Category: animal | Type: PRESCRIPTION ANIMAL DRUG LABEL
Date: 20251028

ACTIVE INGREDIENTS: Helium 990 mL/1 L

helium

PACKAGE LABEL

HELIUM, COMPRESSED USP UN1046 NON-FLAMMABLE GAS 2 Rx Only.
Rx only. WARNING: Administration of Helium may be hazardous or contraindicated. For use only by or under the supervision of a licensed practitioner who is experienced in the use and administration of Helium and is familiar with the indications, effects, dosages, methods, and frequency and duration of administration, and with the hazards, contraindications, and side effects and the precautions to be taken.
WARNING: CONTAINS GAS UNDER PRESSURE; MAY EXPLODE IF HEATED. MAY DISPLACE OXYGEN AND CAUSE RAPID SUFFOCATION. Do not handle until all safety precautions have been read and understood. Use and store only outdoors or in a well-ventilated place. Use a back flow preventive device in the piping. Use only with equipment rated for cylinder pressure. Close valve after each use and when empty. Protect from sunlight when ambient temperature exceeds 52 degrees C (125 degrees F). Read and follow the Safety Data Sheet (SDS) before use. FIRST AID: IF INHALED: Remove person to fresh air and keep comfortable for breathing. Get medical advice/attention.
CAS 7440-59-7 DO NOT REMOVE THIS PRODUCT LABEL CONTENTS: LTRS. CU. FT.
ALL-GAS THE AERO ALL-GAS COMPANY 3150 MAIN ST. . HARTFORD, CT 06120 (860) 278-AERO (2376)